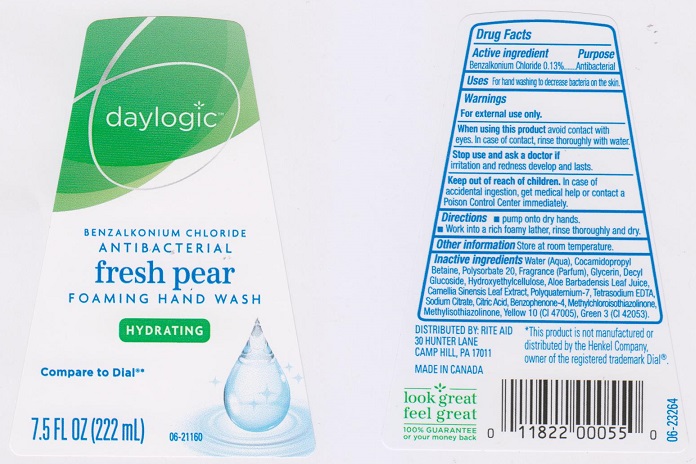 DRUG LABEL: Daylogic Fresh Pear Foaming
NDC: 11822-1090 | Form: SOAP
Manufacturer: Rite Aid Corporation
Category: otc | Type: HUMAN OTC DRUG LABEL
Date: 20170510

ACTIVE INGREDIENTS: BENZALKONIUM CHLORIDE 1.3 mg/1 mL
INACTIVE INGREDIENTS: WATER; COCAMIDOPROPYL BETAINE; POLYSORBATE 20; GLYCERIN; DECYL GLUCOSIDE; HYPROMELLOSES; ALOE VERA LEAF; GREEN TEA LEAF; POLYQUATERNIUM-7 (70/30 ACRYLAMIDE/DADMAC; 1600000 MW); EDETATE SODIUM; SODIUM CITRATE; CITRIC ACID MONOHYDRATE; SULISOBENZONE; METHYLCHLOROISOTHIAZOLINONE; METHYLISOTHIAZOLINONE; FD&C GREEN NO. 3; D&C YELLOW NO. 10

Drug Facts

Active ingredient

Benzalkonium Chloride 0.13%

Purpose

Antibacterial

Uses

for hand washing to decrease bacteria on the skin

Warnings

For external use only.

When using this product

avoid contact with eyes. In case of contact, rinse thoroughly with water.

Stop use and ask a doctor if

irritation and redness develop and lasts.

Keep out of reach of children.

In case of accidental ingestion, get medical help or contact a Poison Control Center immediately.

Directions

- pump onto dry hands
- work into a rich foamy lather, rinse thoroughly and dry

Other information

store at room temperature

Inactive ingredients

Water (Aqua), Cocamidopropyl Betaine, Polysorbate 20, Fragrance (Parfum), Glycerin, Decyl Glucoside, Hydroxyethylcellulose, Aloe Barbadensis Leaf Juice, Camellia Sinensis Leaf Extract, Polyquaternium-7, Tetrasodium EDTA, Sodium Citrate, Citric Acid, Benzophenone-4, Methylchloroisothiazolinone, Methylisothiazolinone, Yellow 10 (CI 47005), Green 3 (CI 42053)